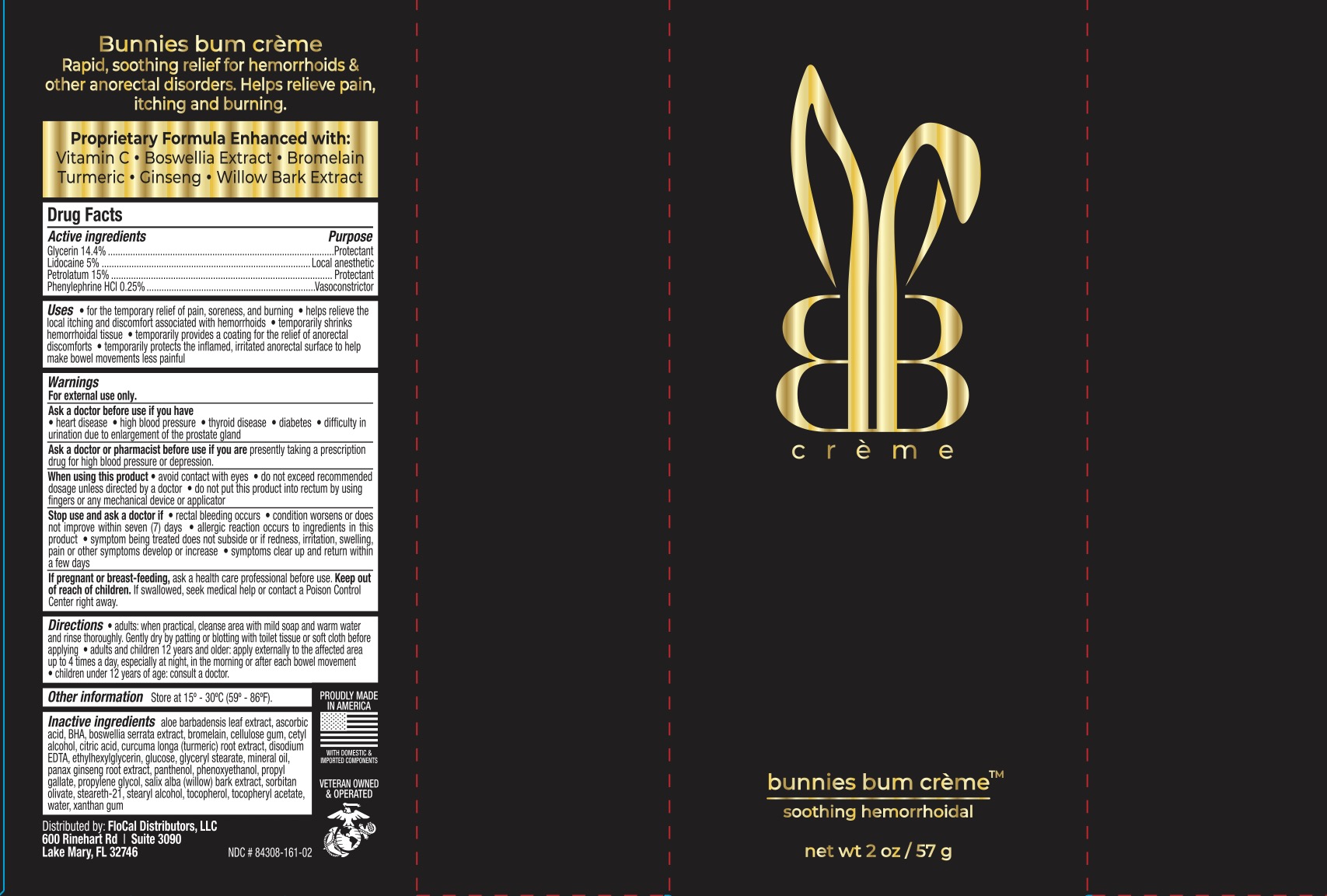 DRUG LABEL: Bunnies Bum Soothing Hemorrhoidal
NDC: 84308-161 | Form: CREAM
Manufacturer: FloCal Distributors LLC
Category: otc | Type: HUMAN OTC DRUG LABEL
Date: 20240705

ACTIVE INGREDIENTS: GLYCERIN 14.4 g/100 g; PETROLATUM 15 g/100 g; PHENYLEPHRINE HYDROCHLORIDE 0.25 g/100 g; LIDOCAINE 5 g/100 g
INACTIVE INGREDIENTS: CITRIC ACID MONOHYDRATE; PROPYL GALLATE; EDETATE DISODIUM; MINERAL OIL; ANHYDROUS DEXTROSE; GLYCERYL MONOSTEARATE; BUTYLATED HYDROXYTOLUENE; PANTHENOL; STEARYL ALCOHOL; CARBOXYMETHYLCELLULOSE SODIUM; TOCOPHEROL; CETYL ALCOHOL; PHENOXYETHANOL; ALOE VERA LEAF; ASCORBIC ACID; INDIAN FRANKINCENSE; .ALPHA.-TOCOPHEROL ACETATE; TURMERIC; PROPYLENE GLYCOL; ASIAN GINSENG; SORBITAN OLIVATE; STEARETH-21; WATER; ETHYLHEXYLGLYCERIN; XANTHAN GUM; BROMELAINS; SALIX ALBA BARK

Bunnies Bum Creme Soothing Hemorrhoidal

ACTIVE INGREDIENT

Glycerin 14.4%, Lidocaine 5%, Petrolatum 15%, Phenylephrine HCl 0.25%

PURPOSE

Glycerin-Protectant

Lidocaine-Local anesthetic

Petrolatum-Protectant

Phenylephrine HCl Vasoconstrictor

INDICATIONS AND USAGE

- For the temporary relief of pain, soreness, and burning
- Helps relieve the local itching and discomfort associated with hemorrhoids
- Temporarily shrinks hemorrhoidal tissue
- Temporarily provides a costing for the relief of anorectal discomforts
- Temporarily protects the inflamed, irritated anorectal surface to help make bowel movements less painful

WARNINGS

For external use only.

Ask a doctor before use if you have

- heart disease
- high blood pressure
- thyroid disease
- diabetes
- difficulty in urination due to enlargement of the prostate gland

Ask a doctor or pharmacist before use if you are presently taking a prescription drug for high blood pressure or depression

When using this product

- avoid contact with eyes
- do not exceed recommended dosage unless directed by a doctor
- do not put this into the rectum by using fingers or any mechanical device or applicator

Stop use and ask a doctor if

- rectal bleeding occurs
- condition worsens or does not improve within 7 days
- allergic reaction occurs to ingredients in this product
- symptom being treated does not subside or if redness, irritation, swelling, pain or other symptoms develop or increase
- symptoms clear up and return within a few days

PREGNANCY OR BREAST FEEDING

Ask a health professional before use.

KEEP OUT OF REACH OF CHILDREN

If swallowed, get medical help or contact a Poison Control Center right away.

DOSAGE AND ADMINISTRATION

- Adults: when practical, clean area with mild soap and warm water and rinse thoroughly. Gently dry by patting or blotting with toilet tissue or soft cloth before applying.
- Adults and children 12 years and older: apply externally to the affected area up to 4 times a day, especially at night, in the morning, or after each bowel movement.
- Children under 12 years of age: consult a doctor.

INACTIVE INGREDIENT

Aloe barbadensis leaf extract, ascorbic acid, BHT, boswellia serrata extract, bromelain, cellulose gum, cetyl alcohol, citric acid, curcuma long (turmeric) root extract, disodium EDTA, ethylhexylglycerin, glucose, glyceryl stearate, mineral oil, panax ginseng root extract, panthenol, phenoxyethanol, propyl gallate, propylene glycol, salix alba (willow) bark extract, sorbitan olivate, steareth-21, stearyl alcohol, tocopherol, tocopheryl acetate, water, xanthan gum.